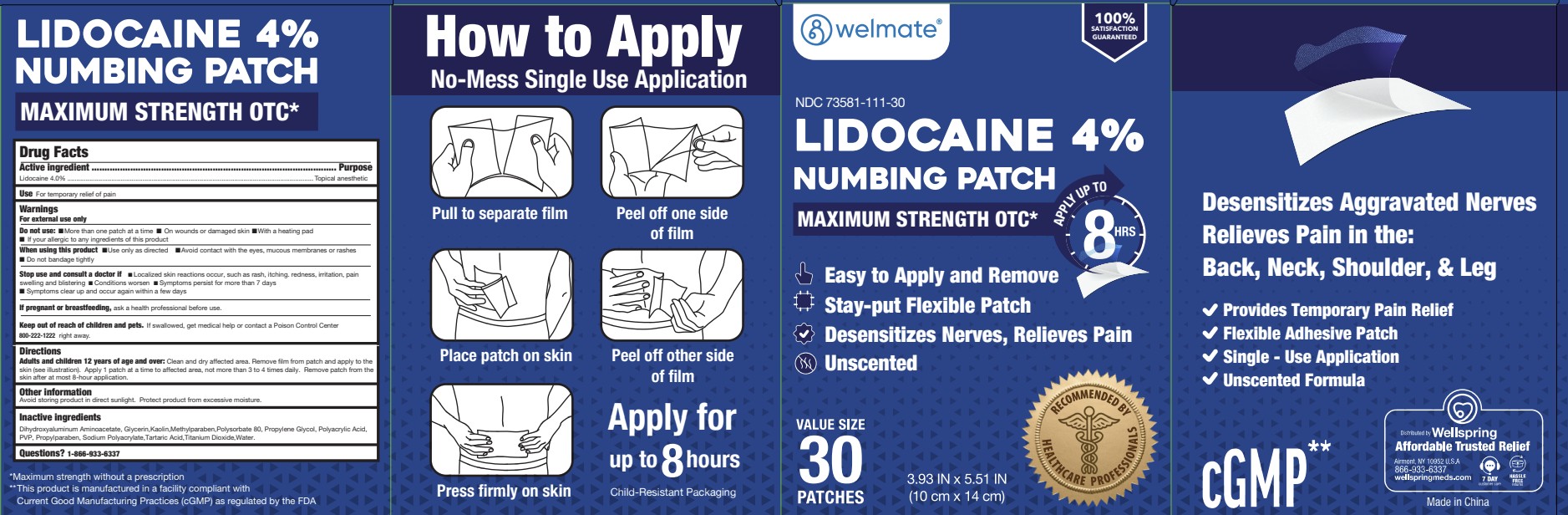 DRUG LABEL: Welmate Lidocaine Pain Relieving Patch
NDC: 73581-912 | Form: PATCH
Manufacturer: YYBA CORP
Category: otc | Type: HUMAN OTC DRUG LABEL
Date: 20260209

ACTIVE INGREDIENTS: LIDOCAINE 0.04 g/1 g
INACTIVE INGREDIENTS: TARTARIC ACID; TITANIUM DIOXIDE; PROPYLENE GLYCOL; POLYSORBATE 80; KAOLIN; WATER; PROPYLPARABEN; GLYCERIN; POVIDONE; DIHYDROXYALUMINUM AMINOACETATE; SODIUM POLYACRYLATE (8000 MW); POLYACRYLIC ACID (250000 MW); METHYLPARABEN

YYBA Lidocaine Patch C

ACTIVE INGREDIENTS

Lidocaine 4.0%

PURPOSE

Topical anesthetic

USES

Temporarily relieves minor pain

WARNINGS

For external use only

WARNINGS

Do not use

- More than one patch on your body at a time
- On cut, irritated or swollen skin
- On puncture wounds
- For more than one week without consulting a doctor
- If you are allergic to any active or inactive ingredients
- If pouch is damaged or opened

When using this product

- Use only as directed
- Read and follow all directions and warnings on this pack
- Do not allow contact with the eyes
- Do not use at the same time as other topical analgesics
- Do not bandage tightly or apply local heat (such as heating pads) to the area of use
- Do not microwave
- Dispose of used patch in manner that always keeps product away from children and pets
- Used patches still contain the drug product that can produce serious adverse effects if a child or pet chews or ingests this patch

Stop use and ask a doctor if

- Condition worsens
- Redness is present Irritation develops
- Symptoms persist for more than 7 days or clear up and occur again within a few days
- You experience signs of skin injury, such as pain, swelling or blistering where the product was applied

If pregnant or breast-feeding

- ask a health professional before use.

Keep out of reach of children.

If swallowed, get medical help or contact a Poison Control Center (1-800-222-1222) right away.

DIRECTIONS

Adults and children over 12 years: Clean and dry affected area. Remove film from patch (see illustration). Apply sticky side of patch to affected area. Use one patch for up to 12 hours. Discard patch after single use

Children 12 years of age or younger: Consult a physician.

OTHER INFORMATION

Store in a clean, dry place outside of direct sunlight. Protect from excessive moisture.

INACTIVE INGREDIENTS

aluminum glycinate, glycerin, kaolin, methylparaben, polyacrylic acid, polysorbate 80, propylene glycol, propylparaben, PVP, sodium polyacrylate, tartaric acid, titanium dioxide, water

Questions? 1-866-933-6337